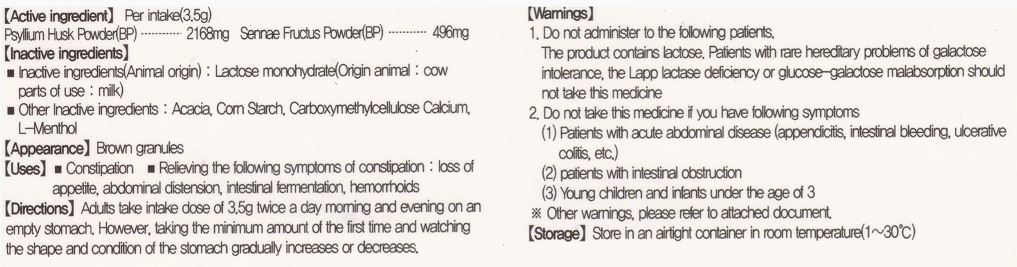 DRUG LABEL: LAXATIVES RUBILAX
NDC: 72988-0010 | Form: GRANULE
Manufacturer: Lydia Co., Ltd.
Category: otc | Type: HUMAN OTC DRUG LABEL
Date: 20231216

ACTIVE INGREDIENTS: PSYLLIUM HUSK 2168 mg/3.5 g; SENNA PODS 496 mg/3.5 g
INACTIVE INGREDIENTS: LEVOMENTHOL; LACTOSE MONOHYDRATE

Drug Facts

ACTIVE INGREDIENT

psyllium husk powder, sennae fructus powder

INACTIVE INGREDIENT

lactose monohydrate, acacia, corn starch, carboxymethylcellulose calcium, l-menthol

PURPOSE

constipation

relieving the following symptoms of constipation: loss of appetite, abdominal distension, intestinal fermentation, hemorrhoids

keep out of reach of the children

INDICATIONS AND USAGE

adults take intake does of 3.5g twice a day morning and evening on an empty stomach, however, taking the minimum amount of the first time and watching the shape and condition of the stomach gradually increases or decreases

WARNINGS

do not administer to the following patients,

the product contains lactose, patients with rare hereditary problems of galactose intolerance, the lapp deficiency or glucose-galactose malabsorption should not take this medicine

DOSAGE AND ADMINISTRATION

for oral use only